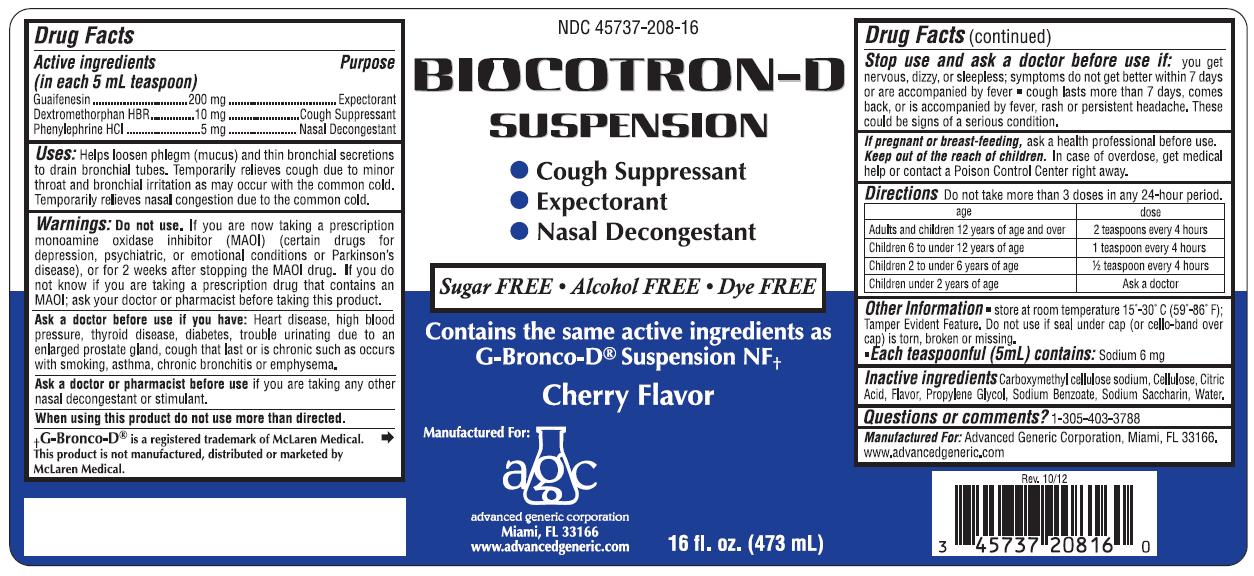 DRUG LABEL: Biocotron-D
NDC: 45737-208 | Form: SUSPENSION/ DROPS
Manufacturer: Advanced Generic Corporation
Category: otc | Type: HUMAN OTC DRUG LABEL
Date: 20241220

ACTIVE INGREDIENTS: DEXTROMETHORPHAN HYDROBROMIDE 10 mg/5 mL; GUAIFENESIN 200 mg/5 mL; PHENYLEPHRINE HYDROCHLORIDE 5 mg/5 mL
INACTIVE INGREDIENTS: CITRIC ACID MONOHYDRATE; CARBOXYMETHYLCELLULOSE SODIUM; POWDERED CELLULOSE; SODIUM BENZOATE; PROPYLENE GLYCOL; SACCHARIN SODIUM; WATER

AGC-BiocotronDSus 208

Active Ingredients (in each 5mL) Purpose

Dextromethorphan HBr, 10 mg ................................. Cough Suppressant

Guaifenesin, 200 mg ................................................ Expectorant

Phenylephrine HCl, 5 mg ...................................... Nasal Decongestant

Uses

Helps loosen phlegm (mucus) and thin bronchial secretions to drain bronchial tubes. Temporarily relieves cough due to minor throat and bronchial irritation as may occur with the common cold. Temporarily relieves nasal congestion due to the common cold.

Warnings:

Ask a doctor before use if you have:

Heart disease, high blood pressure, thyroid disease, diabetes, trouble urinating due to an enlarged prostate gland, cough that last or is chronic such as occurs with smoking, asthma, chronic bronchitis or emphysema.
Ask doctor or pharmacist before useif you are taking any other nasal decongestant or stimulant.
When using this product do not use more than directed.

PREGNANCY OR BREAST FEEDING

If pregnant or breast-feeding,ask a health professional before use.

Do not use.

If you are now taking a prescription monoamine oxidase inhibitor (MAOI) (certain drugs for depression, psychiatric or emotional conditions, or Parkinson's disease), or for 2 weeks after stopping the MAOI drug. If you do not know if you are taking a prescription drug that contains an MAOI, ask a doctor or pharmacist before taking this product.
Stop use and ask a doctor before use if:

- you get nervous, dizzy or sleepless; symptoms do not get better within 7 or are accompanied by fever
- cough lasts more than 7 days, comes back, or is accompanied by fever, rash or persistent headache. These could be signs of a serious condition.

KEEP OUT OF REACH OF CHILDREN

Keep out of the reach of children.In case of accidental overdose, get medical help or contact a Poison Control Center right away.

DOSAGE AND ADMINISTRATION

Directions:Do not take more than 3 doses in any 24-hour period.

Age | Dose
Adults and children 12 years of age and over | 2 teaspoons every 4 hours
Children 6 to under 12 years of age | 1 teaspoon every 4 hours
Children 2 to under 6 years of age | 1/2 teaspoon every 4 hours
Children under 2 years of age | Ask a doctor

INACTIVE INGREDIENT

Inactive ingredients:Carboxymethyl cellulose sodium, Cellulose, Citric Acid, Flavor, Propylene Glycol, Sodium Benzoate, Sodium Saccharin, Water

Questions or comments?1-305-403-3788

Other information:Store at room temperature 15-30 degrees C (59-86 degrees F)

Tamper evident:Do not use if seal under cap (or cello-band over cap) is torn, broken or missing.

Each teaspoonful (5mL) contains:Sodium 6 mg